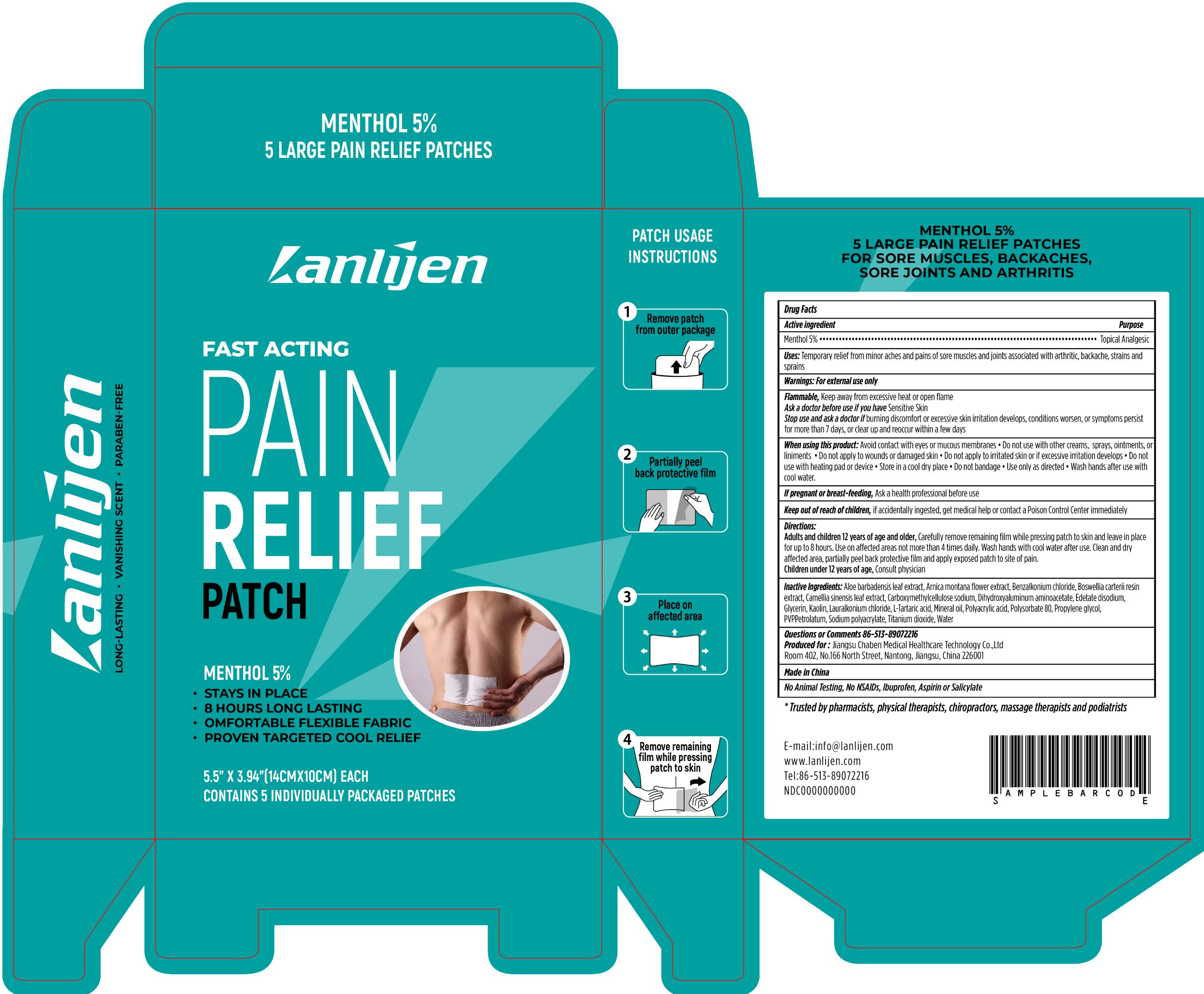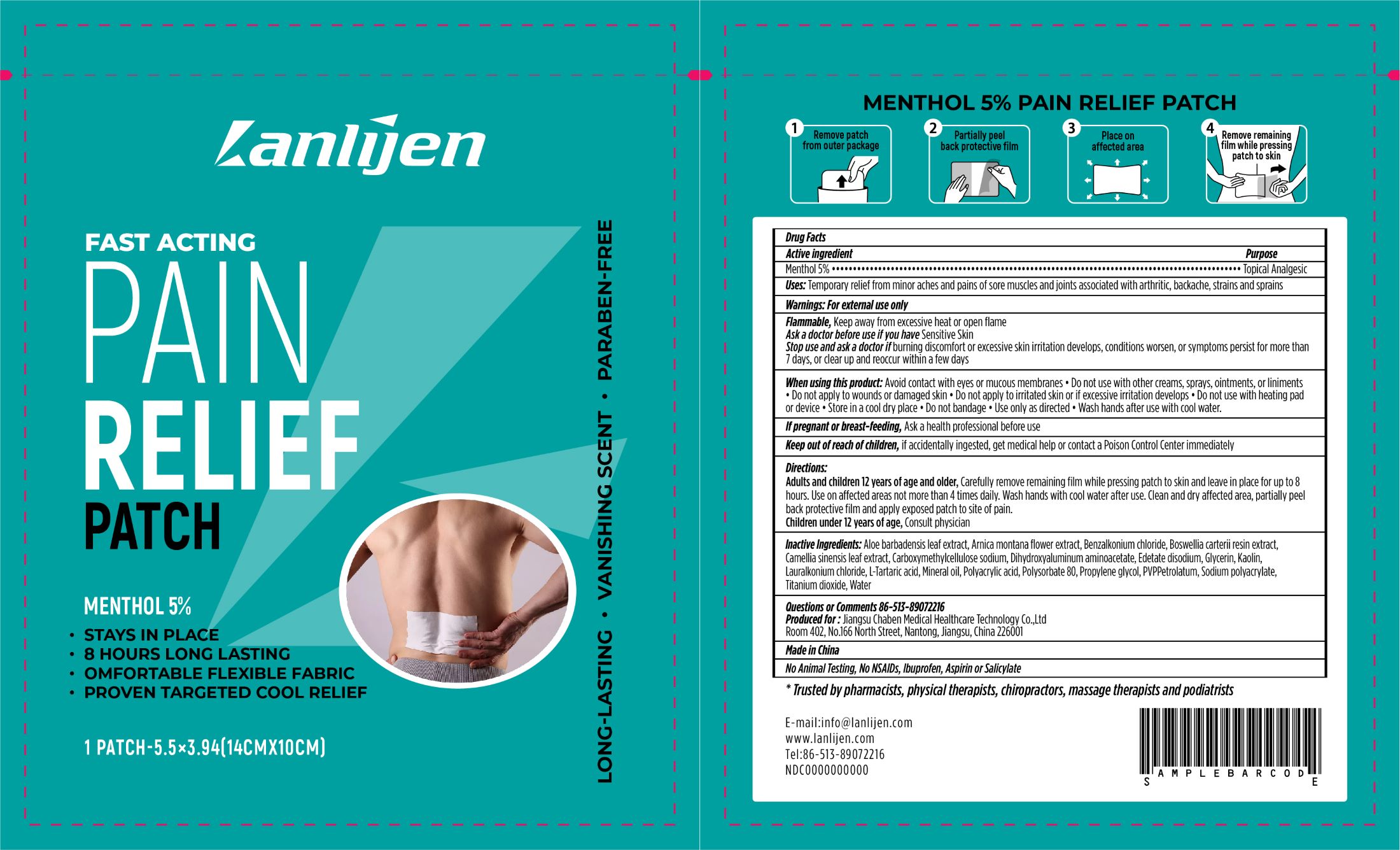 DRUG LABEL: Lanlijen Menthol Pain Relief
NDC: 83050-251 | Form: PATCH
Manufacturer: Jiangsu Chaben Medical Healthcare Technology Co.,Ltd
Category: otc | Type: HUMAN OTC DRUG LABEL
Date: 20221213

ACTIVE INGREDIENTS: MENTHOL 0.05 g/1 g
INACTIVE INGREDIENTS: PETROLATUM; POLYACRYLIC ACID (250000 MW); WATER; BENZALKONIUM CHLORIDE; CARBOXYMETHYLCELLULOSE SODIUM; DIHYDROXYALUMINUM AMINOACETATE ANHYDROUS; EDETATE DISODIUM; KAOLIN; ALOE VERA LEAF; ARNICA MONTANA FLOWER; GLYCERIN; FRANKINCENSE; BENZODODECINIUM CHLORIDE; GREEN TEA LEAF; TARTARIC ACID; MINERAL OIL; PROPYLENE GLYCOL; POLYSORBATE 80; POVIDONE K90; SODIUM POLYACRYLATE (2500000 MW); TITANIUM DIOXIDE

Lanlijen, Menthol Pain Relief, 5, Patch

Active ingredient

Menthol 5.0% w/w ...... Purpose: Topical Analgesic

Purpose

Topical Analgesic

Uses

Temporary relief from minor aches and pains of sore muscles and joints associated with arthritic, backache, strains and sprains

Warnings

For external use only

Flammable, Keep away from excessive heat or open flame

Ask a doctor before use if you have Sensitive Skin

Stop use and ask a doctor if burning discomfort or excessive skin irritation develops, conditions worsen, or symptoms persist for more than 7 days, or clear up and reoccur within a few days

Ask a doctor before use if you have Sensitive Skin

Stop use and ask a doctor if burning discomfort or excessive skin irritation develops, conditions worsen, or symptoms persist for more than 7 days, or clear up and reoccur within a few days

Stop use and ask a doctor if burning discomfort or excessive skin irritation develops, conditions worsen, or symptoms persist for more than 7 days, or clear up and reoccur within a few days

When using this product

Avoid contact with eyes or mucous membranes • Do not use with other creams, sprays, ointments, or liniments • Do not apply to wounds or damaged skin • Do not apply to irritated skin or if excessive irritation develops • Do not use with heating pad or device • Store in a cool dry place • Do not bandage • Use only as directed • Wash hands after use with cool water.

• Do not use with other creams, sprays, ointments, or liniments • Do not apply to wounds or damaged skin • Do not apply to irritated skin or if excessive irritation develops • Do not use with heating pad or device

STORAGE AND HANDLING

• Store in a cool dry place

If pregnant or breast-feeding

Ask a health professional before use

Keep out of reach of children

If accidentally ingested, get medical help or contact a Poison Control Center immediately

Directions

Adults and children 12 years of age and older, Carefully remove remaining film while pressing patch to skin and leave in place for up to 8 hours. Use on affected areas not more than 4 times daily. Wash hands with cool water after use. Clean and dry afected areas, partially peel back protective film and apply exposed patch to site of pain.

Children under 12 years of age, Consult physician

ASK DOCTOR/PHARMACIST

Children under 12 years of age, Consult physician

Inactive Ingredients

Aloe barbadensis leaf extract, Arnica montana flower extract, Benzalkonium chloride, Boswellia carterii resin extract, Camellia sinensis leaf extract, Carboxymethylcellulose sodium, Dihydroxyaluminum aminoacetate, Edetate disodium, Glycerin, Kaolin, Lauralkonium chloride, L-Tartaric acid, Mineral oil, Petrolatum, PVP, Polyacrylic acid, Polysorbate 80, Propylene glycol, Sodium polyacrylate, Titanium dioxide, Water

Questions or Comments

86-513-89072216

E-mail:info@lanlijen.com
www.lanlijen.com
Tel:86-513-89072216

OTHER SAFETY INFORMATION

No Animal Testing, No NSAIDs, lbuprofen, Aspirin or Salicylate